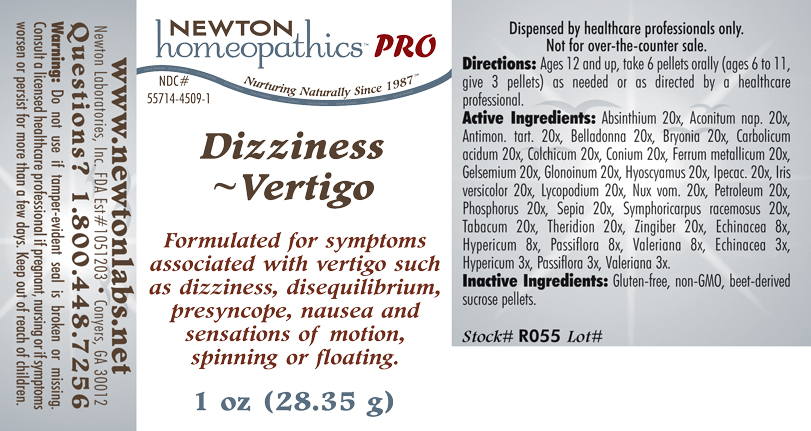 DRUG LABEL: Dizziness  - Vertigo 
NDC: 55714-4509 | Form: PELLET
Manufacturer: Newton Laboratories, Inc.
Category: homeopathic | Type: HUMAN PRESCRIPTION DRUG LABEL
Date: 20110601

ACTIVE INGREDIENTS: Wormwood 20 [hp_X]/1 g; Aconitum Napellus 20 [hp_X]/1 g; Antimony Potassium Tartrate 20 [hp_X]/1 g; Atropa Belladonna 20 [hp_X]/1 g; Bryonia Alba Root 20 [hp_X]/1 g; Phenol 20 [hp_X]/1 g; Colchicum Autumnale Bulb 20 [hp_X]/1 g; Conium Maculatum Flowering Top 20 [hp_X]/1 g; Iron 20 [hp_X]/1 g; Gelsemium Sempervirens Root 20 [hp_X]/1 g; Nitroglycerin 20 [hp_X]/1 g; Hyoscyamus Niger 20 [hp_X]/1 g; Ipecac 20 [hp_X]/1 g; Iris Versicolor Root 20 [hp_X]/1 g; Lycopodium Clavatum Spore 20 [hp_X]/1 g; Strychnos Nux-vomica Seed 20 [hp_X]/1 g; Kerosene 20 [hp_X]/1 g; Phosphorus 20 [hp_X]/1 g; Sepia Officinalis Juice 20 [hp_X]/1 g; Symphoricarpos Albus Fruit 20 [hp_X]/1 g; Tobacco Leaf 20 [hp_X]/1 g; Theridion Curassavicum 20 [hp_X]/1 g; Ginger 20 [hp_X]/1 g; Echinacea, Unspecified 8 [hp_X]/1 g; Hypericum Perforatum 8 [hp_X]/1 g; Passiflora Incarnata Flowering Top 8 [hp_X]/1 g; Valerian 8 [hp_X]/1 g
INACTIVE INGREDIENTS: Sucrose

Dizziness - Vertigo

INDICATIONS & USAGE SECTION

Dizziness - Vertigo Formulated for symptoms associated with vertigo such as dizziness, disequilibrium, presyncope, nausea and sensations of motion, spinning or floating.

DOSAGE & ADMINISTRATION SECTION

Directions: Ages 12 and up, take 6 pellets orally (ages 6 to 11, give 3 pellets) as needed or as directed by a healthcare professional.

ACTIVE INGREDIENT SECTION

Absinthium 20x, Aconitum nap. 20x, Antimon. tart. 20x, Belladonna 20x, Bryonia 20x, Carbolicum acidum 20x, Colchicum 20x, Conium 20x, Ferrum metallicum 20x, Gelsemium 20x, Glonoinum 20x, Hyoscyamus 20x, Ipecac. 20x, Iris versicolor 20x, Lycopodium 20x, Nux vom. 20x, Petroleum 20x, Phosphorus 20x, Sepia 20x, Symphoricarpus racemosus 20x, Tabacum 20x, Theridion 20x, Zingiber 20x, Echinacea 8x, Hypericum 8x, Passiflora 8x, Valeriana 8x, Echinacea 3x, Hypericum 3x, Passiflora 3x, Valeriana 3x.

PURPOSE SECTION

Formulated for symptoms associated with vertigo such as dizziness, disequilibrium, presyncope, nausea and sensations of motion, spinning or floating.

INACTIVE INGREDIENT SECTION

Inactive Ingredients: Gluten-free, non-GMO, beet-derived sucrose pellets.

QUESTIONS? SECTION

www.newtonlabs.net Newton Laboratories, Inc. FDA Est # 1051203 - Conyers, GA 30012
Questions? 1.800.448.7256

WARNINGS SECTION

Warning: Do not use if tamper - evident seal is broken or missing. Consult a licensed healthcare professional if pregnant, nursing or if symptoms worsen or persist for more than a few days. Keep out of reach of children.

PREGNANCY OR BREAST FEEDING SECTION

Consult a licensed healthcare professional if pregnant, nursing or if symptoms worsen or persist for more than a few days.

KEEP OUT OF REACH OF CHILDREN SECTION

Keep out of reach of children.